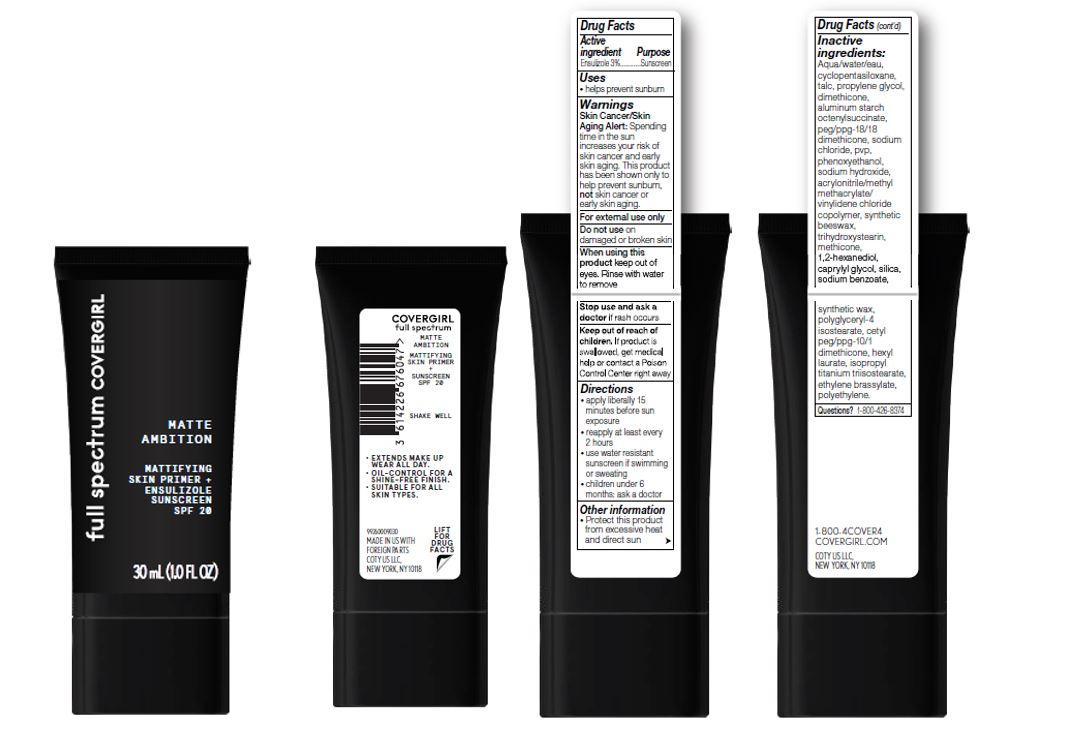 DRUG LABEL: FULL SPECTRUM MATTE AMBITION SKIN PRIMER SPF 20
NDC: 22700-201 | Form: LIQUID
Manufacturer: Noxell Corporation
Category: otc | Type: HUMAN OTC DRUG LABEL
Date: 20241119

ACTIVE INGREDIENTS: ENSULIZOLE 3 g/100 mL
INACTIVE INGREDIENTS: ALUMINUM STARCH OCTENYLSUCCINATE; PEG/PPG-18/18 DIMETHICONE; PHENOXYETHANOL; SODIUM HYDROXIDE; HEXYL LAURATE; ETHYLENE BRASSYLATE; DIMETHICONE; SODIUM CHLORIDE; POLYGLYCERYL-4 ISOSTEARATE; TALC; WATER; CETYL PEG/PPG-10/1 DIMETHICONE (HLB 2); ISOPROPYL TITANIUM TRIISOSTEARATE

Covergirl Full Spectrum Matte Ambition Primer SPF 20

Active ingredient

Ensulizole 3%

Purpose

Sunscreen

Uses

helps prevent sunburn

Warnings

Skin Cancer/Skin Aging Alert: Spending time in the sun increases your risk of skin cancer and early skin aging. This product has been shown only to help prevent sunburn, not skin cancer or early skin aging.

WARNINGS

For external use only.

Do not use on damaged or broken skin

When using this product keep out of eyes. Rinse with water to remove.

Stop use and ask a doctor if rash occurs

Keep out of reach of children. If product is swallowed, get medical help or contact a Poison Control Center right away.

Directions

- apply liberally 15 minutes before sun exposure
- reapply at least every 2 hours
- use water resistant sunscreen if swimming or sweating
- children under 6 months: ask a doctor

Other information

Protect this product from excessive heat and direct sun

Inactive ingredients

Aqua/Water/Eau, Cyclopentasiloxane, Talc, Propylene Glycol, Dimethicone, Aluminum Starch Octenylsuccinate, PEG/PPG-18/18 Dimethicone, Sodium Chloride, PVP, Phenoxyethanol, Sodium Hydroxide, Acrylonitrile/Methyl Methacrylate/Vinylidene Chloride Copolymer, Synthetic Beeswax, Trihydroxystearin, Methicone, 1,2-Hexanediol, Caprylyl Glycol, Silica, Sodium Benzoate, Synthetic Wax, Polyglyceryl-4 Isostearate, Cetyl PEG/PPG-10/1 Dimethicone, Hexyl Laurate, Isopropyl Titanium Triisostearate, Ethylene Brassylate, Polyethylene.

Questions?

1-800-426-8374

PACKAGE LABEL

full spectrum

COVERGIRL

MATTE AMBITION

MATTIFYING

SKIN PRIMER +

ENSULIZOLE

SUNSCREEN

SPF 20

30 mL (1.0 FL OZ)